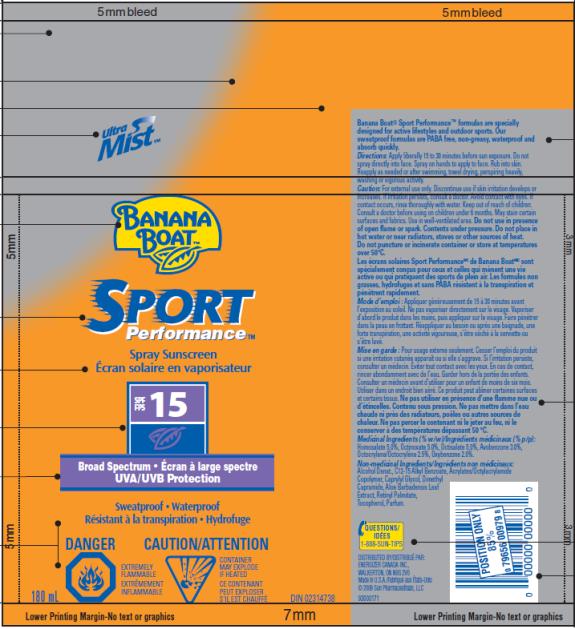 DRUG LABEL: Banana Boat Sport Performance SPF 15 Canada
NDC: 17630-2042 | Form: SPRAY
Manufacturer: Accra-Pac, Inc.
Category: otc | Type: HUMAN OTC DRUG LABEL
Date: 20100328

ACTIVE INGREDIENTS: HOMOSALATE 0.05 mL/1 mL; OCTINOXATE 0.05 mL/1 mL; OCTISALATE 0.05 mL/1 mL; AVOBENZONE 0.03 mL/1 mL; OCTOCRYLENE 0.025 mL/1 mL; OXYBENZONE 0.02 mL/1 mL
INACTIVE INGREDIENTS: C12-15 ALKYL BENZOATE; CAPRYLYL GLYCOL; ALOE VERA LEAF; VITAMIN A PALMITATE

Banana Boat Sport Performance SPF 15 Canada

Active Ingredients

Homosalate 0.05mL / 1mL

Octinoxate 0.05mL / 1mL

Octisalate 0.05mL / 1mL

Avobenzone 0.03mL / 1mL

Octocrylene 0.025mL / 1mL

Oxybenzone 0.02mL / 1mL

Directions:

Apply liberally 15 to 30 minutes before sun exposure. Do not spray directly into face. Spray on hands to apply to face. Rub into skin. Reapply as needed or after swimming, towel drying, perspiring heavily, washing or vigorous activity.

Caution:

For external use only. Discontinue use if skin irritation develops or increases. If irritation persists, consult a doctor. Avoid contact with eyes. If contact occurs, rinse thoroughly with water. Keep out of reach of children. Consult a doctor before using on children under 6 months. May stain certain surfaces and fabrics. Use in well-ventilated area. Do not use in presence of open flame or spark. Contents under pressure. Do not place in hot water or near radiators, stoves or other sources of heat. Do not puncture or incinerate container or store at temperatures over 50ºC.

Mode d’emploi :

Appliquer généreusement de 15 à 30 minutes avant l’exposition au soleil. Ne pas vaporiser directement sur le visage. Vaporiser d’abord le produit dans les mains, puis appliquer sur le visage. Faire pénétrer dans la peau en frottant. Réappliquer au besoin ou après une baignade, une forte transpiration, une activité vigoureuse, s’être séché à la serviette ou s’être lavé.

Mise en garde :

Pour usage externe seulement. Cesser l’emploi du produit si une irritation cutanée apparaît ou si elle s’aggrave. Si l’irritation persiste, consulter un médecin. Éviter tout contact avec les yeux. En cas de contact, rincer abondamment avec de l’eau. Garder hors de la portée des enfants. Consulter un médecin avant d’utiliser pour un enfant de moins de six mois. Utiliser dans un endroit bien aéré. Ce produit peut abîmer certaines surfaces et certains tissus. Ne pas utiliser en présence d’une flamme nue ou d’étincelles. Contenu sous pression. Ne pas mettre dans l’eau chaude ni près des radiateurs, poêles ou autres sources de chaleur. Ne pas percer le contenant ni le jeter au feu, ni le conserver à des températures dépassant 50 °C.

Medicinal Ingredients (% w/w)/Ingrédients médicinaux (% p/p):

Homosalate 5.0%, Octinoxate 5.0%, Octisalate 5.0%, Avobenzone 3.0%, Octocrylene/Octocrylène 2.5%, Oxybenzone 2.0%.

Non-medicinal Ingredients/Ingrédients non médicinaux:

Alcohol Denat., C12-15 Alkyl Benzoate, Acrylates/Octylacrylamide Copolymer, Caprylyl Glycol, Dimethyl Capramide, Aloe Barbadensis Leaf Extract, Retinyl Palmitate,Tocopherol, Parfum.

QUESTIONS/IDÉES

1-888-SUN-TIPS

DISTRIBUTED BY/DISTRIBUÉ PAR:
ENERGIZER CANADA INC.,
WALKERTON, ON N0G 2V0
Made in U.S.A./Fabriqué aux États-Unis
© 2009 Sun Pharmaceuticals, LLC

PRINCIPAL DISPLAY PANEL

UltraMist TM
BANANA
BOATTM
SPORT
Performance TM
Spray Sunscreen
Écran solaire en vaporisateur
SPF/FPS 15
Broad Spectrum Écran à large spectre
UVA/UVB Protection
Sweatproof Waterproof
Résistant à la transpiration Hydrofuge
180 mL